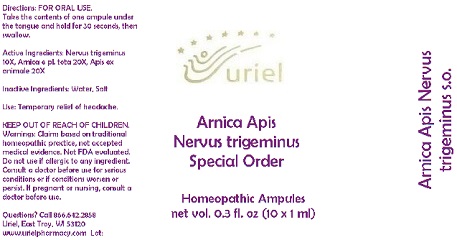 DRUG LABEL: Arnica Apis Nervus trigeminus Special Order
NDC: 48951-1227 | Form: LIQUID
Manufacturer: Uriel Pharmacy Inc.
Category: homeopathic | Type: HUMAN OTC DRUG LABEL
Date: 20191126

ACTIVE INGREDIENTS: BOS TAURUS NERVE 10 [hp_X]/1 mL; ARNICA MONTANA 20 [hp_X]/1 mL; APIS MELLIFERA 20 [hp_X]/1 mL
INACTIVE INGREDIENTS: WATER; SODIUM CHLORIDE

Arnica Apis Nervus trigeminus Special Order

INDICATIONS AND USAGE

Directions: FOR ORAL USE.

DOSAGE AND ADMINISTRATION

Take the contents of one ampule under the tongue and hold for 30 seconds, then swallow.

ACTIVE INGREDIENT

Active Ingredients: Nervus trigeminus 10X, Arnica e pl. tota 20X, Apis ex animale 20X

Inactive Ingredients: Water, Salt

PURPOSE

Use: Temporary relief of headache.

KEEP OUT OF REACH OF CHILDREN.

WARNINGS

Warnings: Claims based on traditional homeopathic practice, not accepted medical evidence. Not FDA evaluated. Do not use if allergic to any ingredient. Consult a doctor before use for serious conditions or if conditions worsen or persist. If pregnant or nursing, consult a doctor before use.

QUESTIONS

Questions? Call 866.642.2858 Uriel, East Troy, WI 53120 www.urielpharmacy.com